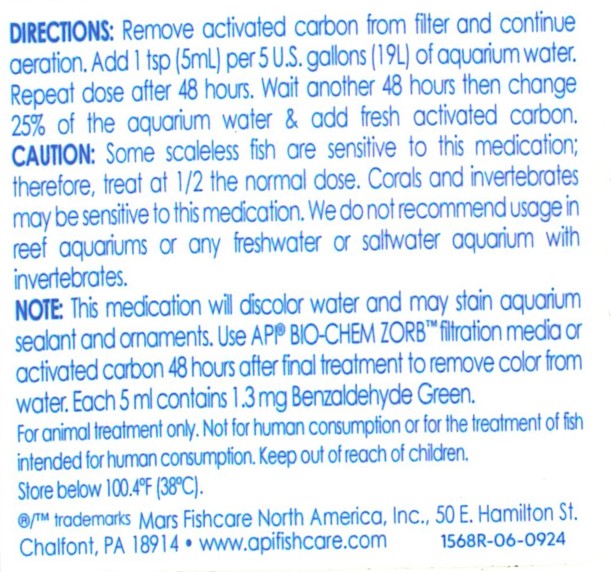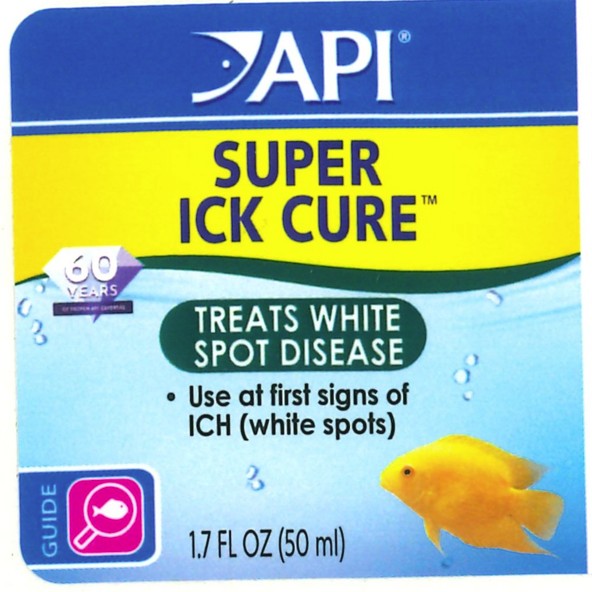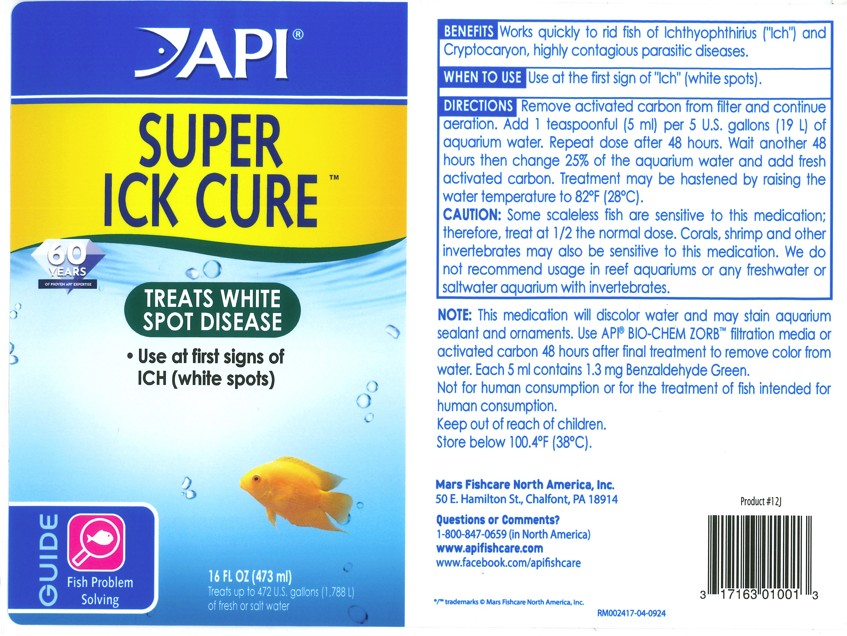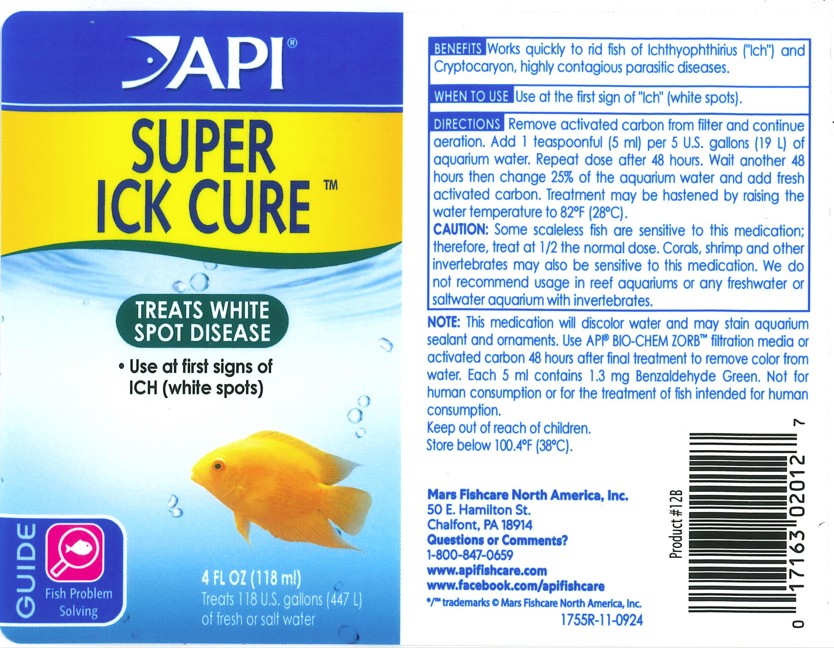 DRUG LABEL: API Super Ick Cure
NDC: 17163-514 | Form: LIQUID
Manufacturer: MARS FISHCARE NORTH AMERICA, INC.
Category: animal | Type: OTC ANIMAL DRUG LABEL
Date: 20251120

ACTIVE INGREDIENTS: MALACHITE GREEN 1.3 mg/5 mL
INACTIVE INGREDIENTS: WATER

Drug Label

ACTIVE INGREDIENT

Each 5 ml contains 1.3 mg Benzaldehyde Green

DOSAGE AND ADMINISTRATION

DIRECTIONS: Remove activated carbon from filter and continue aeration. Add 1 teasponful (5 ml) per 5 U.S. gallons (19 L) of aquarium water. Repeat dose after 48 hours. Wait another 48 hours then change 25% of the aquarium water and add fresh activated carbon. Treatment may be hastened by raising the water temperatureto 82 F (28 C)

WARNINGS AND PRECAUTIONS

CAUTION: Some scaleless fish are sensitive to this medication; therefore, treat at 1/2 the normal dose. Corals, Shrimp and other invertebrates may also be sensitive to thi medication. We do not recommend usage in reef aquariums or any freshwateror saltwater aquarium with invertebrates.

Note: This medication will discolor water and may stain aquarium sealant and ornaments. Use API BIO-CHEM ZORB or activated carbon 48 hours after final treatment to remove color from water. Each 5 ml contains 1.3 mg Benzaldehyde Green.

Not for human consumption or for the treatment of fish intended for human consumption. Keep out or reach of children. Store below 100.4ºF (38ºC).

PACKAGE LABEL

API

SUPER

ICK CURE

TREATS WHITE

SPOT DISEASE

Use at first signs of

ICH (white spots)

Guide

Fish Problem

Solving

4 FL OZ (118 ml)

Treats 118 U.S. gallons (447 L)

of fresh or salt water